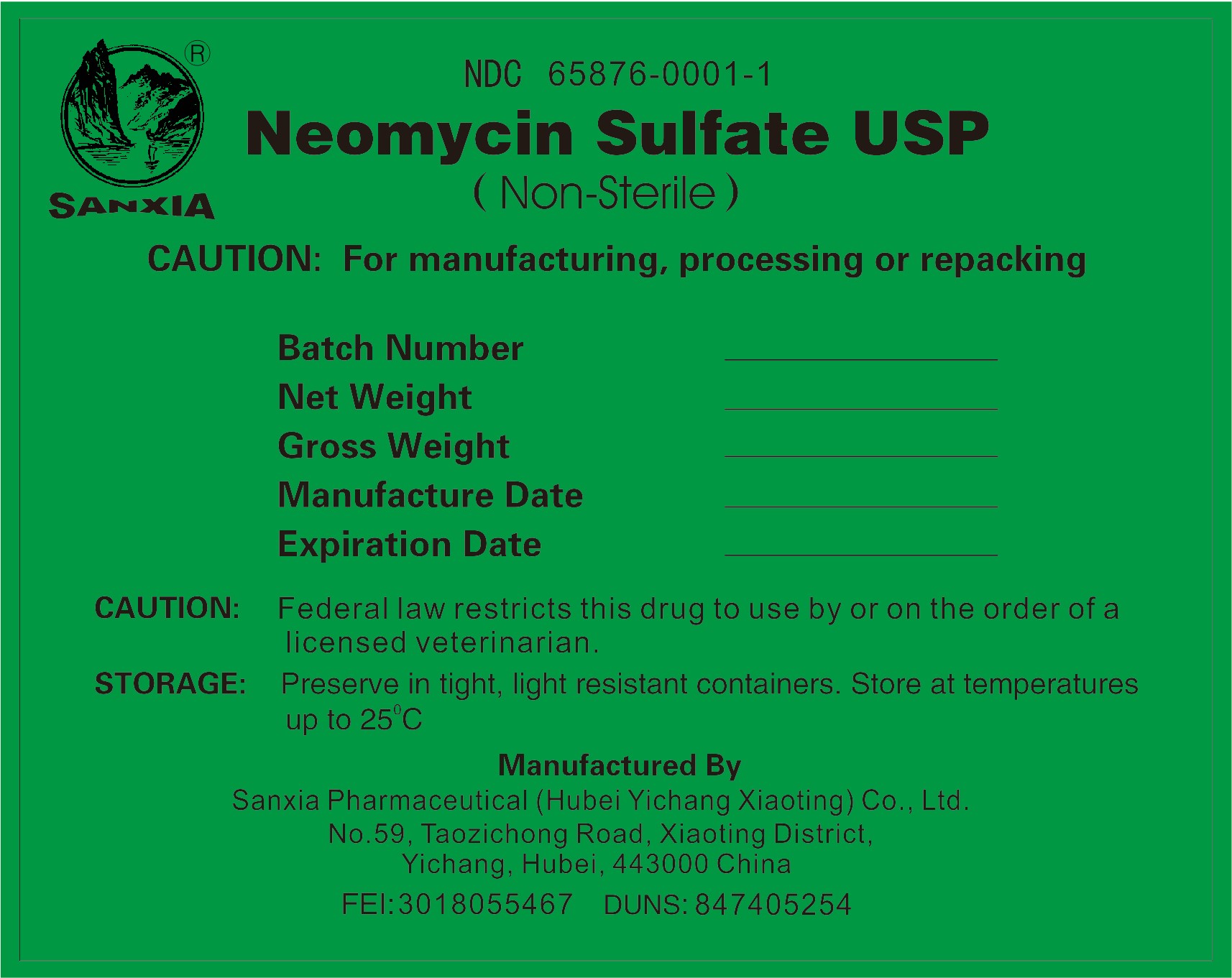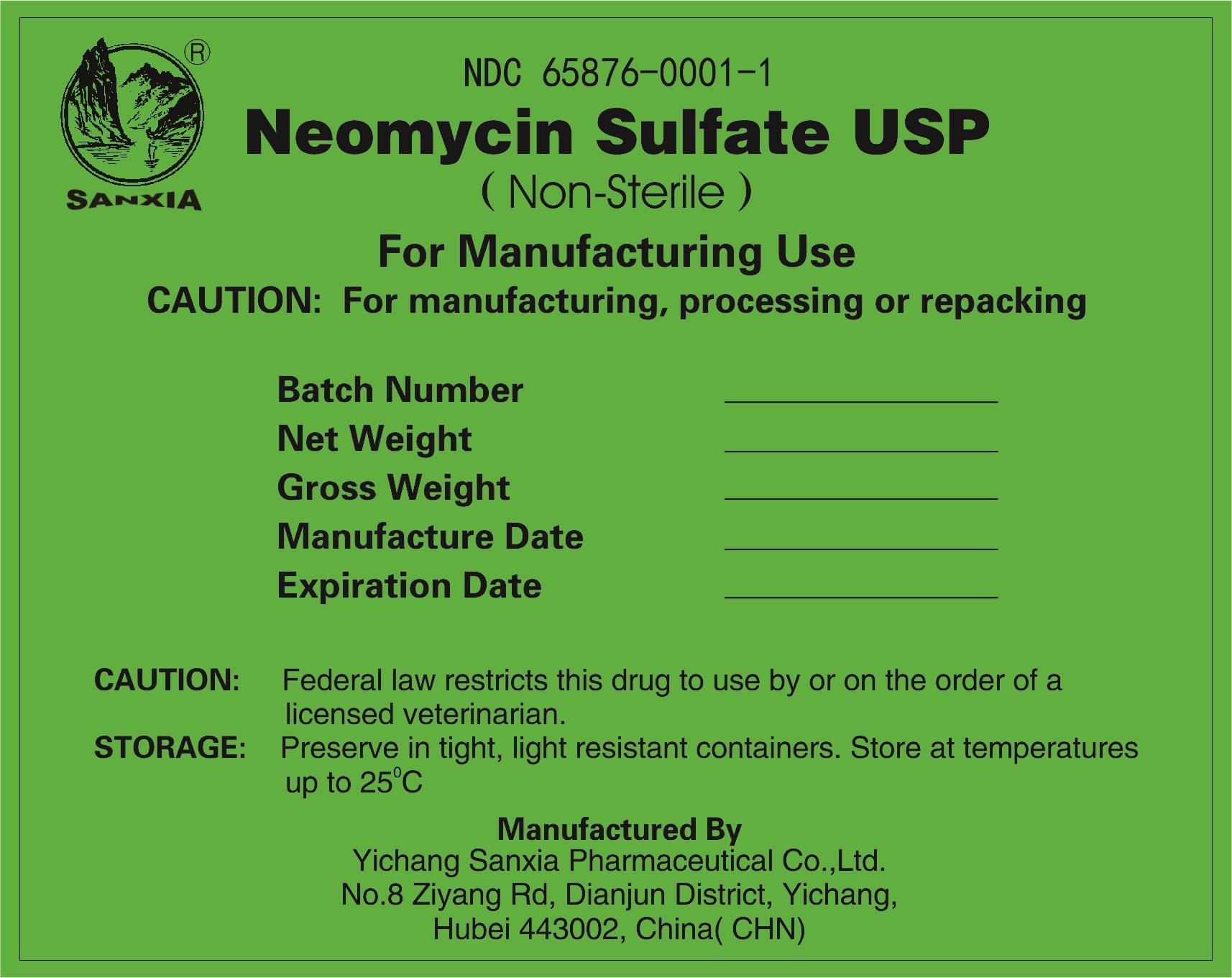 DRUG LABEL: Neomycin Sulfate
NDC: 65876-0001 | Form: POWDER
Manufacturer: Yichang Sanxia Pharmaceutical Co., Ltd.
Category: other | Type: BULK INGREDIENT - ANIMAL DRUG
Date: 20251223

ACTIVE INGREDIENTS: Neomycin Sulfate 1 kg/1 kg

Neomycin Sulfate